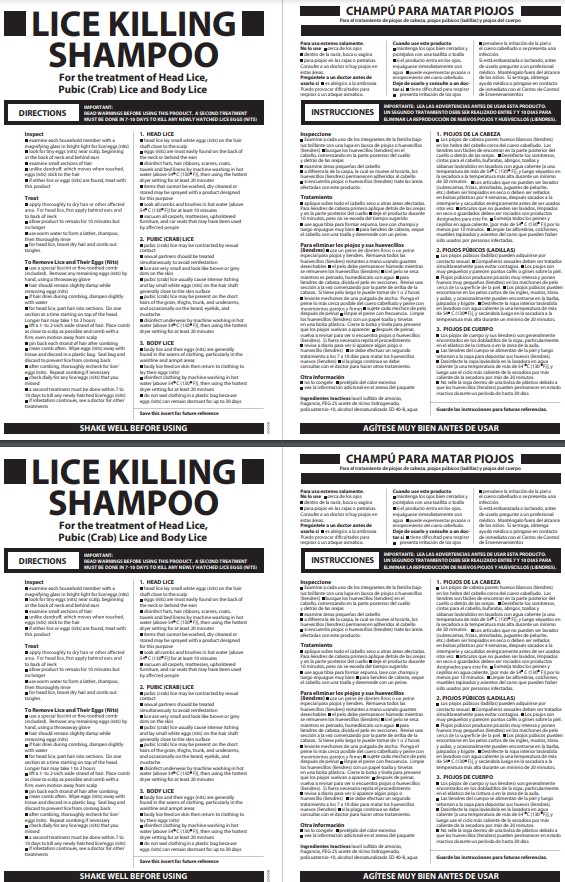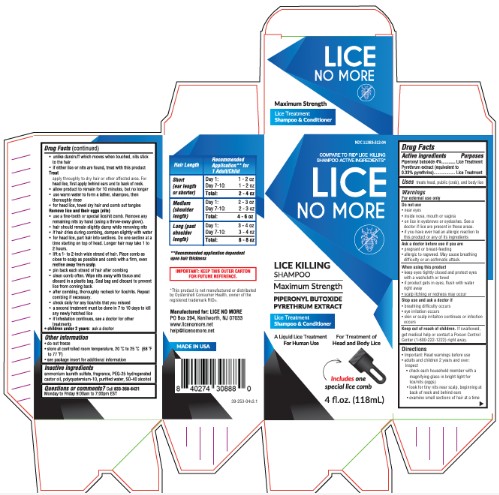 DRUG LABEL: Lice No More Lice Killing
NDC: 11383-001 | Form: SHAMPOO
Manufacturer: Weeks & Leo Co., Inc
Category: otc | Type: HUMAN OTC DRUG LABEL
Date: 20250609

ACTIVE INGREDIENTS: PIPERONYL BUTOXIDE 4 g/100 mL; PYRETHRUM EXTRACT 0.33 g/100 mL
INACTIVE INGREDIENTS: AMMONIUM LAURETH-3 SULFATE; WATER; POLYQUATERNIUM-10 (400 CPS AT 2%); PEG-25 HYDROGENATED CASTOR OIL; ALCOHOL

ACTIVE INGREDIENT

Piperonyl butoxide 4%

Pyrethrum extract (equivalent to 0.33% pyrethrins)

PURPOSE

Lice treatment

WARNINGS

For external use only

ASK DOCTOR

- pregnant or breastfeeding
- allergic to ragweed. May cause breathing difficulty or an asthmatic attack.

DO NOT USE

- near eyes
- inside nose, mouth, or vagina
- on lice in eyebrows or eyelashes. See a doctor if lice are present in these areas.

WHEN USING

- keep eyes tightly closed and protect eyes with a washcloth or towel
- if product gets into eyes, flush with water right away
- scalp itching or redness may occur

STOP USE

- breathing difficulty occurs
- eye irritation occurs
- skin or scalp irritation continues or infection occurs

KEEP OUT OF REACH OF CHILDREN

If swallowed, get medical help or contact a Poison Control Center (1-800-222-1222) right away.

INDICATIONS AND USAGE

treats head, pubic (crab), and body lice

- Important: Read warnings before use
- Adults and children 2 years and over:

Inspect

- check each household member with a magnifying glass in bright light for lice/nits (eggs)
- look for tiny nits near scalp, beginning at back of neck and behind ears
- examine small sections of hair at a time
- unlike dandruff which moves when touched, nits stick to the hair
- if either lice or nits are found, treat with this product

Treat

- apply thoroughly to DRY HAIR or other affected area. For head lice, first apply behind ears and to back of neck.
- allow product to remain for 10 minutes, but no longer
- use warm water to form a lather, shampoo, then thoroughly rinse
- for head lice, towel dry hair and comb out tangles

Remove lice and their eggs (nits)

- use a fine-tooth or special lice/nit comb. Remove any remaining nits by hand (using a throw-away glove).
- hair should remain slightly damp while removing nits
- if hair dries during combing, dampen slightly with water
- for head lice, part hair into sections. Do one section at a time starting on top of the head. Longer hair may take 1 to 2 hours.
- lift a 1-to 2-inch wide strand of hair. Place comb as close to scalp as possible and comb with a firm, even motion away from scalp.
- pin back each strand of hair after combing
- clean comb often. Wipe nits away with tissue and discard in a plastic bag. Seal bag and discard to prevent lice from coming back.
- after combing, thoroughly recheck for lice/nits. Repeat combing if necessary.
- check daily for any lice/nits that you missed

a second treatment must be done in 7 to 10 days to kill any newly hatched lice

- if infestation continues, see a doctor for other treatments
- Children under 2 years: ask a doctor

QUESTIONS

Call 833-356-6431 Monday to Friday 9:00 am to 7:00 pm EST

INACTIVE INGREDIENT

ammonium laureth sulfate, fragrance, PEG-25 hydrogenated castor oil, polyquaternium-10, purified water, SD-40 alcohol

OTHER SAFETY INFORMATION

- do not freeze
- store at controlled room temperature 20°-25°C (68°-77°F)
- to report serious side effects due to the use of this product call (515) 276-1586
- see package insert for additional information

DOSAGE AND ADMINISTRATION

Treat

apply thoroughly to DRY HAIR or other affected area. For head lice, first apply behind ears and to back of neck.
allow product to remain for 10 minutes, but no longer
use warm water to form a lather, shampoo, then thoroughly rinse
for head lice, towel dry hair and comb out tangles

PACKAGE LABEL

includes comb